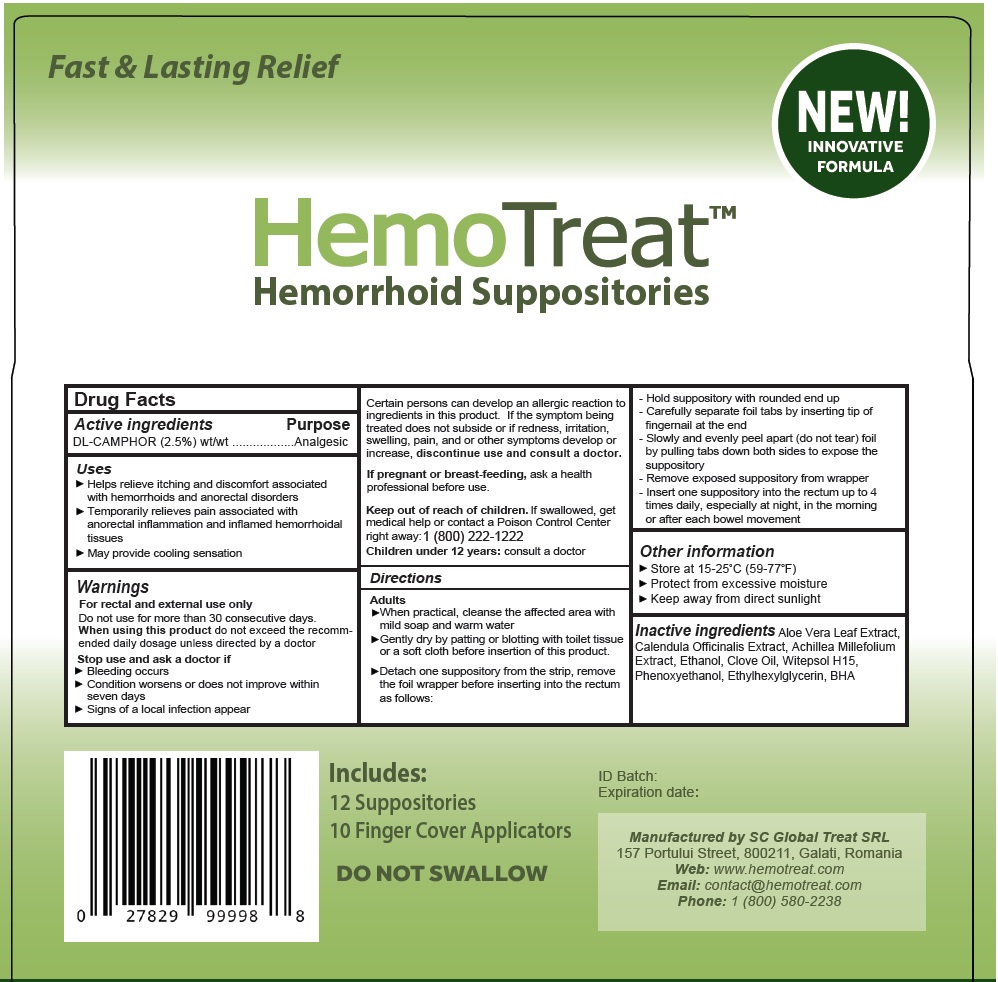 DRUG LABEL: HemoTreat
NDC: 69758-328 | Form: SUPPOSITORY
Manufacturer: Global Treat srl
Category: otc | Type: HUMAN OTC DRUG LABEL
Date: 20201202

ACTIVE INGREDIENTS: CAMPHOR (SYNTHETIC) 0.025 g/1 g
INACTIVE INGREDIENTS: ALOE VERA LEAF; CALENDULA OFFICINALIS FLOWER; ACHILLEA MILLEFOLIUM OIL; ALCOHOL; CLOVE OIL; HYDROGENATED COCO-GLYCERIDES; PHENOXYETHANOL; ETHYLHEXYLGLYCERIN; BUTYLATED HYDROXYANISOLE

HemoTreat (69758-328)

Active Ingredients

DL-CAMPHOR (2.5%) wt/wt

Purposes

Analgesic

Uses

- Helps relieve itching and discomfort associated with hemorrhoids and anorectal disorders
- Temporarily relieves pain associated with anorectal inflammation and inflamed hemorrhoidal tissues
- May provide cooling sensation

Warnings

For rectal use only

Do not use for more than 30 consecutive days

When using this product do not exceed the recommended daily dosage, unless directed by a doctor

Stop use and ask a doctor if:

- Bleeding occurs
- Condition worsens or does not improve within seven days
- Signs of a local infection appear
- Certain person can develop allergic reactions to ingredients in this product. If the symptom being treated does not subside of if redness, irritation, swelling, pain, and or other symptoms develop or increase, discontinue use and consult a doctor.

PREGNANCY OR BREAST FEEDING

If pregnant or breast-feeding, ask a health professional before use.

KEEP OUT OF REACH OF CHILDREN

Keep out of the reach of children. If swallowed, get medical help or contact a poison Control Center right away 1 (800) 222-1222.

Children under 12 years: consult a doctor

Directions

Adults

- When practical, cleanse the affected area with mild soap and warm water
- Gently dry by patting or blotting with toilet tissue or a soft cloth before insertion of this product.
- Detach one suppository from the strip, remove the foil wrapper before inserting into the rectum as follows:
  - Hold suppository with rounded end up
  - Carefully separate foil tabs by inserting tip of fingernail at the end
  - Slowly and evenly peel apart (do not tear) foil by pulling tabs down both sides to expose the suppository
  - Remove exposed suppository from wrapper
  - Insert one suppository into the rectum up to 4 times daily, especially at night, in the morning or after each bowel movement

Other Information

- Store at 15-25°C (59-77°F)
- Protect from excessive moisture
- Keep away from direct sunlight

Inactive Ingredients

Aloe Vera Leaf Extract, Calendula Officinalis Extract, Achillea Millefolium Extract, Ethanol, Clove Oil, Witepsol H15, Phenoxyethanol, Ethylhexylglycerin, BHA

QUESTIONS

Manufactured by SC Global Treat SRL

157 Portului Street, 800211, Galati, Romania

Web: www.hemotreat.com

EMail: contact@hemotreat.com

Questions? Call: 1 (800) 580-2238

Principal Display Panel

NDC 69758-328-88

HemoTreat

Hemorrhoidal Suppositories